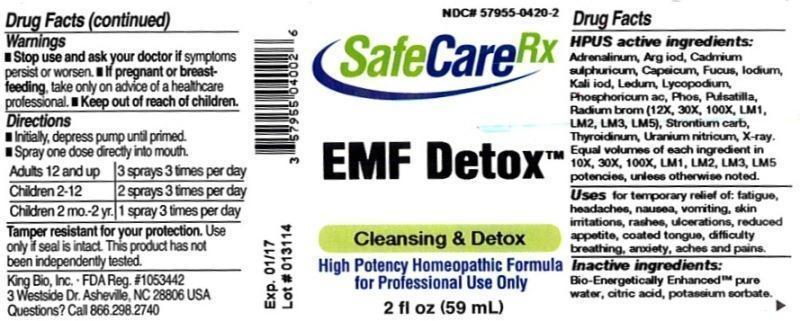 DRUG LABEL: EMF Detox
NDC: 57955-0420 | Form: LIQUID
Manufacturer: King Bio Inc.
Category: homeopathic | Type: HUMAN OTC DRUG LABEL
Date: 20140417

ACTIVE INGREDIENTS: EPINEPHRINE 10 [hp_X]/59 mL; SILVER IODIDE 10 [hp_X]/59 mL; CADMIUM SULFATE 10 [hp_X]/59 mL; CAPSICUM 10 [hp_X]/59 mL; FUCUS VESICULOSUS 10 [hp_X]/59 mL; IODINE 10 [hp_X]/59 mL; POTASSIUM IODIDE 10 [hp_X]/59 mL; LEDUM PALUSTRE TWIG 10 [hp_X]/59 mL; LYCOPODIUM CLAVATUM SPORE 10 [hp_X]/59 mL; PHOSPHORIC ACID 10 [hp_X]/59 mL; PHOSPHORUS 10 [hp_X]/59 mL; PULSATILLA VULGARIS 10 [hp_X]/59 mL; RADIUM BROMIDE 12 [hp_X]/59 mL; STRONTIUM CARBONATE 10 [hp_X]/59 mL; THYROID, UNSPECIFIED 10 [hp_X]/59 mL; URANYL NITRATE HEXAHYDRATE 10 [hp_X]/59 mL; ALCOHOL, X-RAY EXPOSED (1000 RAD) 10 [hp_X]/59 mL
INACTIVE INGREDIENTS: WATER; CITRIC ACID MONOHYDRATE; POTASSIUM SORBATE

EMF Detox™

ACTIVE INGREDIENT

Drug Facts__________________________________________________________________________________________________________

HPUS activeingredients: Adrenalinum, Argentum iodatum, Cadmium sulphuricum,Capsicum annuum, Fucus vesiculosus, Iodium, Kali iodatum, Ledum palustre, Lycopodium clavatum, Phosphoricum acidum, Phosphorus, Pulsatilla, Radium bromatum (12X, 30X, 100X, LM1, LM2, LM3, LM5) Strontium carbonicum, Thyroidinum, Uranium nitricum, X-ray . Equal volumes of each ingredient in 10X, 30X, 100X, LM1, LM2, LM3, LM5 potencies, unless otherwise noted.

INDICATIONS AND USAGE

Uses for temporary relief of: fatigue, headaches, nausea, vomiting, skin irritations, rashes, ulcerations, reduced appetite, coated tongue, difficulty breathing, anxiety, aches and pains.

Inactive Ingredients:

Bio-Energetically Enhanced™ pure water, citric acid and potassium sorbate.

Warnings

- Stop use and ask your doctor if symptoms persist or worsen.
- If pregnant or breast-feeding, take only on advice of a healthcare professional.

- Keep out of reach of children

Directions

- Initially, depress pump until primed.
- Spray one dose directly into mouth.
- Adults 12 and up: 3 sprays 3 times per day.
- Children 2-12: 2 sprays 3 times per day.
- Children 2 mo.-2 yr.: 1 spray 3 times per day.

OTHER SAFETY INFORMATION

Tamper resistant for your protection. Use only if seal is intact. This product has not been independently tested.

PURPOSE

Uses for temporary relief of:

- fatigue
- headaches
- nausea
- vomiting
- skin irritations
- rashes
- ulcerations
- reduced appetite
- coated tongue
- difficulty breathing
- anxiety
- aches and pains